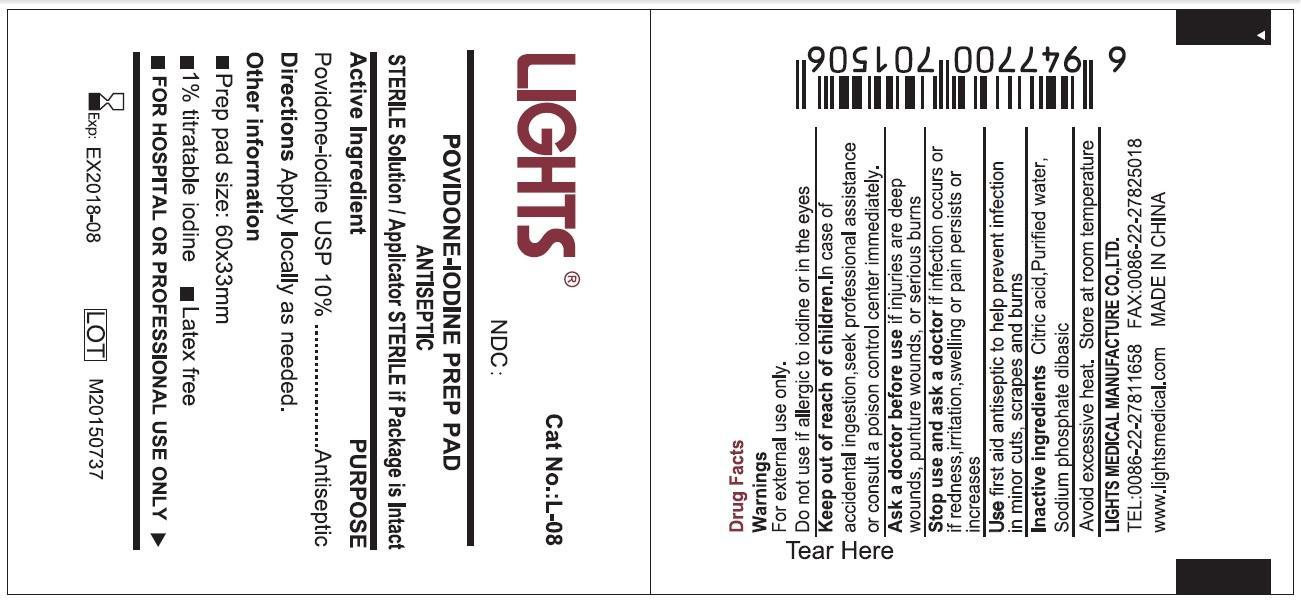 DRUG LABEL: Lights  Povidone Iodine Prep Pad
NDC: 61333-203 | Form: SOLUTION
Manufacturer: Lights Medical Manufacture Co., Ltd.
Category: otc | Type: HUMAN OTC DRUG LABEL
Date: 20260121

ACTIVE INGREDIENTS: POVIDONE-IODINE 1 g/100 g
INACTIVE INGREDIENTS: WATER; CITRIC ACID MONOHYDRATE; SODIUM PHOSPHATE, DIBASIC

61333-203

Active Ingredient: Povidone-Iodine USP (10%)

Purpose: Antiseptic

Use:

First aid antiseptic to help prevent infection in minor cuts, scrapes and burns.

Warnings:

For external use only

Do not use if allergic to iodine or in the eyes

Keep out of reach of children. In case of accidental ingestion, seek professional assistance or consult a poison control center immediately

Ask a doctor before use if injuries are deep wounds, puncture wounds or serious burns

Stop use and ask a doctor if infection occurs or if redness, irritation, swelling, or pain persists or increases

DOSAGE AND ADMINISTRATION

Apply locally as need

Other information

- 1% available iodine
- latex free
- for hospital or professional use only

Inactive Ingredient

Citric acid, purified water, Sodium phosphate dibasic